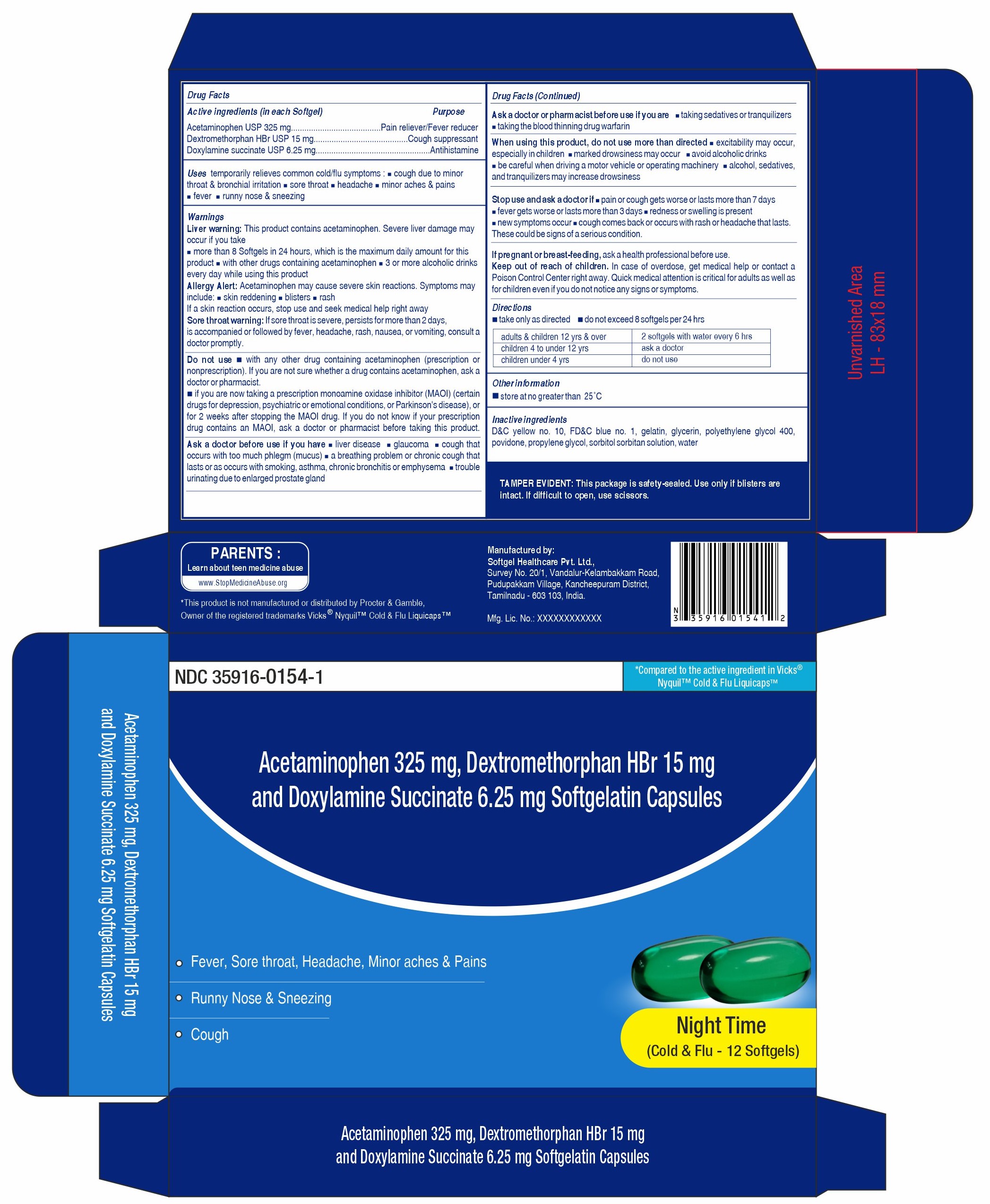 DRUG LABEL: Acetaminophen, Dextromethorphan Hydrobromide and Doxylamine Succinate
NDC: 35916-0154 | Form: CAPSULE, LIQUID FILLED
Manufacturer: Softgel Healthcare Private Limited
Category: otc | Type: HUMAN OTC DRUG LABEL
Date: 20260128

ACTIVE INGREDIENTS: ACETAMINOPHEN 325 mg/1 1; DOXYLAMINE SUCCINATE 6.25 mg/1 1; DEXTROMETHORPHAN HYDROBROMIDE 15 mg/1 1
INACTIVE INGREDIENTS: GLYCERIN; SORBITOL; WATER; GELATIN; POVIDONE; POLYETHYLENE GLYCOL 400; D&C YELLOW NO. 10; PROPYLENE GLYCOL; FD&C BLUE NO. 1

Acetaminophen 325 mg, Dextromethorphan Hydrobromide 15mg and Doxylamine Succinate 6.25 mg Softgelatin Capsules (Night time)

Active ingredients(in each Softgel)

Acetaminophen USP 325 mg

Dextromethorphan HBr USP 15 mg

Doxylamine succinate USP 6.25 mg

Purpose

Pain reliever/Fever reducer

Cough suppressant

Antihistamine

Uses

temporarily relieves common cold/flu symptoms:

- cough due to minor throat & bronchial irritation
- sore throat
- headache
- minor aches & pains
- fever
- runny nose & sneezing

Warnings

Liver warning:

This product contains acetaminophen.Severe liver damage may occur if you take

- more than 8 softgels in 24 hours, which is the maximum daily amount for this product
- with other drugs containing acetaminophen
- 3 or more alcoholic drinks every day while using this product

Allergy Alert:

Acetaminophen may cause severe skin reactions. Symptoms may include:

- skin reddening
- blisters
- rash

If a skin reaction occurs, stop use and seek medical help right away

Sore throat warning:

If sore throat is severe, persists for more than 2 days,is accompanied or followed by fever, headache, rash, nausea or vomiting, consult a doctor promptly.

Do not use

- with any other drug containing acetaminophen (prescription or nonprescription). If you are not sure whether a drug contains acetaminophen, ask a doctor or pharmacist.
- if you are now taking a prescription monoamine oxidase inhibitor (MAOI) (certain drugs for depression, psychiatric or emotional conditions, or Parkinson's disease), or for 2 weeks after stopping the MAOI drug. If you do not know if your prescription drug contains an MAOI, ask a doctor or pharmacist before taking this product.

Ask a doctor before use if you have

- liver disease
- glaucoma
- cough that occurs with too much phlegm (mucus)
- a breathing problem or chronic cough that lasts or as occurs with smoking, asthma, chronic bronchitis or emphysema
- trouble urinating due to enlarged prostate gland

Ask a doctor or pharmacist before use if you are

- taking sedatives or tranquilizers
- taking the blood thinning drug warfarin

When using this product

- do not use more than directed
- excitability may occur, especially in children
- marked drowsiness may occur
- avoid alcoholic drinks
- be careful when driving a motor vehicle or operating machinery
- alcohol, sedatives, & tranquilizers may increase drowsiness

Stop use and ask a doctor if

- pain or cough gets worse or lasts more than 7 days
- fever gets worse or lasts more than 3 days
- redness or swelling is present
- new symptoms occur
- cough comes back or occurs with rash or headache that lasts.

These could be signs of a serious condition.

If pregnant or breast-feeding

ask a health professional before use.

Keep out of reach of children

In case of overdose, get medical help or contact a Poison Control Center right away. Quick medical attention is critical for adults as well as for children even if you do not notice any signs or symptoms.

Directions

- take only as directed
- do not exceed 8 softgels per 24 hrs

adults & children 12 yrs & over | 2 softgels with water every 6 hrs
children 4 to under 12 yrs | ask a doctor
children under 4 yrs | do not use

Other information

- store at no greater than 25ºC

Inactive ingredients

D&C yellow no. 10, FD&C blue no. 1, gelatin, glycerin, polyethylene glycol 400, povidone, propylene glycol, sorbitol sorbitan solution, water

TAMPER EVIDENT

This package is safety-sealed. Use only if blisters are intact. If difficult to open, use scissors.

Manufactured by

Softgel Healthcare Pvt Ltd.,

Survey no. 20/1, Vandalur-Kelambakkam Road,

Pudupakkam Village, Kancheepuram District,

Tamilnadu – 603103, India

Mfg. Lic. No: xxxxxxxxxxxxxx

PRINCIPAL DISPLAY PANEL

NDC Code: 35916-0154-1

*Compared to the active ingredient in VICKS® NyQuilTM Cold & F LiquicapsTM

Acetaminophen 325 mg, Dextromethorphan Hbr 15 mg and Doxylamine Succinate 6.25 mg Softgelatin Capsules

Fever, Sore Throat, Headache, Minor Aches & Pains

Runny Nose & Sneezing

Cough

Night time

(Cold & Flu - 12 Softgels)